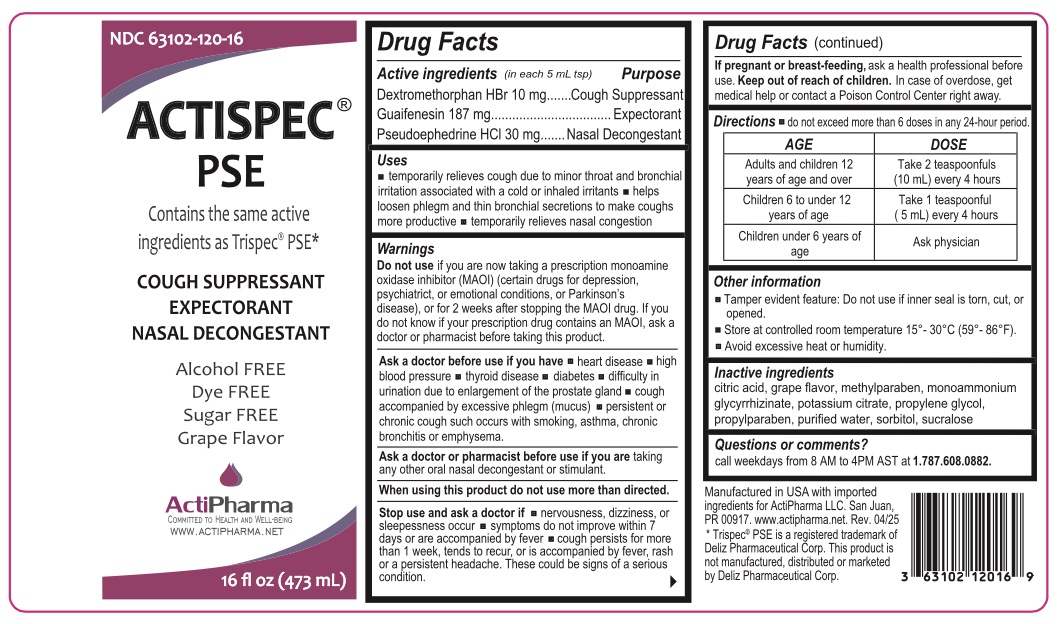 DRUG LABEL: ACTISPEC PSE
NDC: 63102-120 | Form: SOLUTION
Manufacturer: ACTIPHARMA, LLC
Category: otc | Type: HUMAN OTC DRUG LABEL
Date: 20250717

ACTIVE INGREDIENTS: DEXTROMETHORPHAN HYDROBROMIDE 10 mg/5 mL; GUAIFENESIN 187 mg/5 mL; PSEUDOEPHEDRINE HYDROCHLORIDE 30 mg/5 mL
INACTIVE INGREDIENTS: CITRIC ACID MONOHYDRATE; METHYLPARABEN; AMMONIUM GLYCYRRHIZATE; POTASSIUM CITRATE; PROPYLENE GLYCOL; PROPYLPARABEN; WATER; SORBITOL; SUCRALOSE

ACTISPEC® PSE COUGH SUPPRESSANT EXPECTORANT NASAL DECONGESTANT

Active ingredients (in each 5 mL tsp)

Dextromethorphan HBr 10 mg

Guaifenesin 187 mg

Pseudoephedrine HCl 30 mg

Purpose

Cough Suppressant
Expectorant
Nasal Decongestant

Uses

• temporarily relieves cough due to minor throat and bronchial irritation associated with a cold or inhaled irritants • helps loosen phlegm and thin bronchial secretions to make coughs more productive • temporarily relieves nasal congestion

Warnings

Do not use if you are now taking a prescription monoamine oxidase inhibitor (MAOI) (certain drugs for depression, psychiatric, or emotional conditions, or Parkinson’s disease), or for 2 weeks after stopping the MAOI drug. If you do not know if your prescription drug contains an MAOI, ask a doctor or pharmacist before taking this product.

Ask a doctor before use if you have • heart disease • high blood pressure • thyroid disease • diabetes • difficulty in urination due to enlargement of the prostate gland • cough accompanied by excessive phlegm (mucus) • persistent or chronic cough such occurs with smoking, asthma, chronic bronchitis or emphysema.

Ask a doctor or pharmacist before use if you are taking any other oral nasal decongestant or stimulant.

When using this product do not use more than directed.

Stop use and ask a doctor if • nervousness, dizziness or sleeplessness occur • symptoms do not improve within 7 days or are accompanied by fever • cough persists for more than 1 week, tends to recur, or is accompanied by fever, rash, or a persistent headache. These could be signs of a serious condition.

If pregnant or breast-feeding, ask a health professional before use.

Keep out of reach of children. In case of overdose, get medical help or contact a Poison Control Center right away.

Directions

do not exceed more than 6 doses in any 24-hour period.

AGE | DOSE
Adults and children 12 years of age and over | Take 2 teaspoonfuls (10 mL) every 4 hours
Children 6 to under 12 years of age | Take 1 teaspoonful (5 mL) every 4 hours
Children under 6 years of age | Ask physician

Other information

• Tamper evident feature: Do not use if inner seal is torn, cut, or opened.

• Store at controlled room temperature 15° - 30°C (59° - 86°F).

• Avoid excessive heat or humidity.

Inactive ingredients

citric acid, grape flavor, methylparaben, monoammonium glycyrrhizinate, potassium citrate, propylene glycol, propylparaben, purified water, sorbitol, sucralose

Questions or comments?

call weekdays from 8 AM to 4PM AST at 1.787.608.0882.

Contains the same active ingredients as Trispec® PSE*

Alcohol FREE

Dye FREE

Sugar FREE

Grape Flavor

Manufactured in USA with imported ingredients for ActiPharma LLC. San Juan, PR 00917. www.actipharma.net. Rev. 04/25

* Trispec® PSE is a registered trademark of Deliz Pharmaceutical Corp. This product is not manufactured, distributed or marketed by Deliz Pharmaceutical Corp.